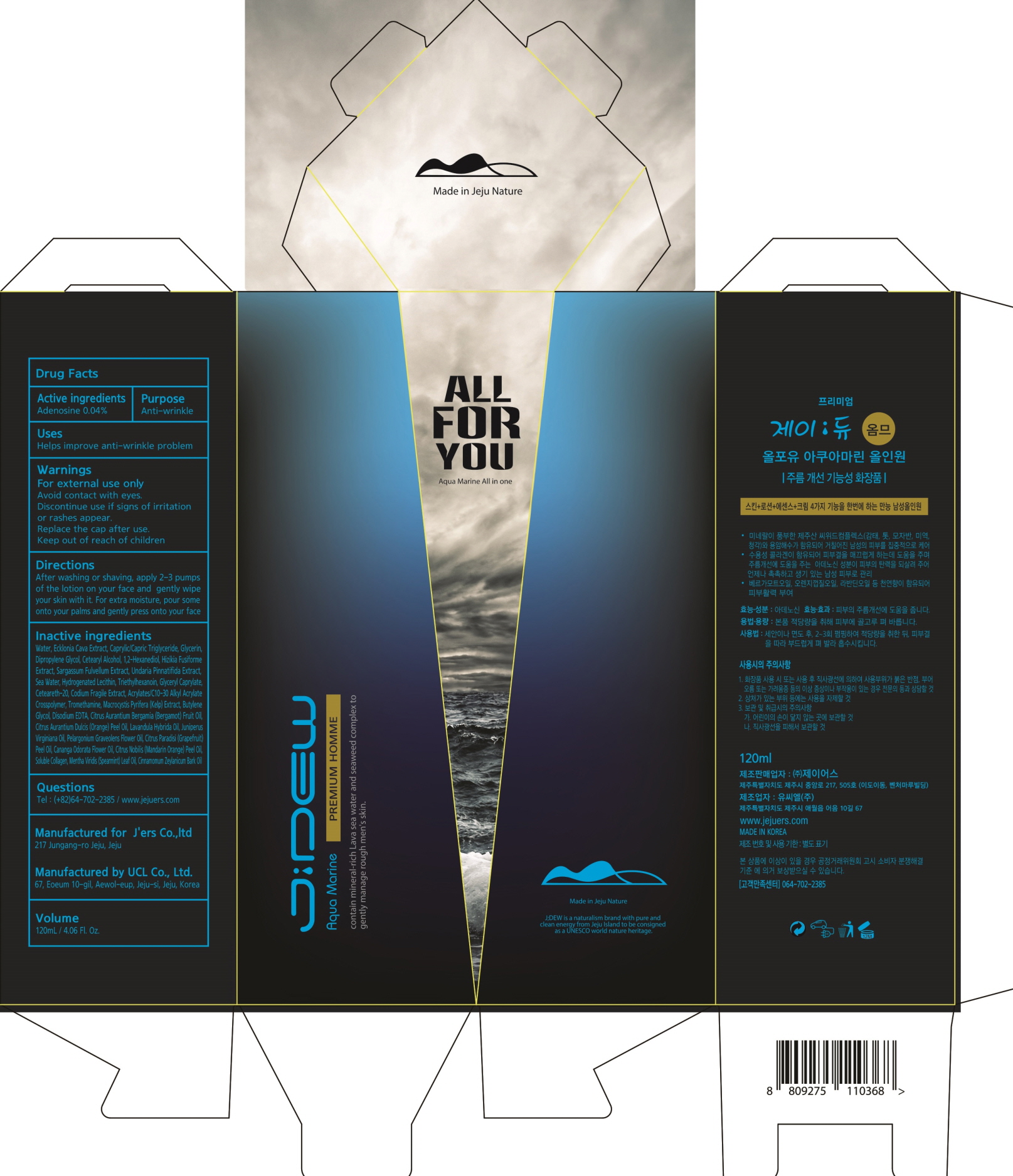 DRUG LABEL: JDEW HOMME ALL FOR YOU AQUA MARINE ALL IN ONE
NDC: 72543-010 | Form: CREAM
Manufacturer: J'ers Co.,ltd
Category: otc | Type: HUMAN OTC DRUG LABEL
Date: 20180918

ACTIVE INGREDIENTS: Adenosine 0.04 g/120 mL
INACTIVE INGREDIENTS: WATER; ECKLONIA CAVA

ACTIVE INGREDIENT

Active ingredients: Adenosine 0.04%

INACTIVE INGREDIENT

Inactive ingredients:

Water, Ecklonia Cava Extract, Caprylic/Capric Triglyceride, Glycerin, Dipropylene Glycol, Cetearyl Alcohol, 1,2-Hexanediol, Hizikia Fusiforme Extract, Sargassum Fulvellum Extract, Undaria Pinnatifida Extract, Sea Water, Hydrogenated Lecithin, Triethylhexanoin, Glyceryl Caprylate, Ceteareth-20, Codium Fragile Extract, Acrylates/C10-30 Alkyl Acrylate Crosspolymer, Tromethamine, Macrocystis Pyrifera (Kelp) Extract, Butylene Glycol, Disodium EDTA, Citrus Aurantium Bergamia (Bergamot) Fruit Oil, Citrus Aurantium Dulcis (Orange) Peel Oil, Lavandula Hybrida Oil, Juniperus Virginiana Oil, Pelargonium Graveolens Flower Oil, Citrus Paradisi (Grapefruit) Peel Oil, Cananga Odorata Flower Oil, Citrus Nobilis (Mandarin Orange) Peel Oil, Soluble Collagen, Mentha Viridis (Spearmint) Leaf Oil, Cinnamomum Zeylanicum Bark Oil

PURPOSE

Purpose: Anti-wrinkle

WARNINGS

- For external use only

- Avoid contact with eyes.

- Discontinue use if signs of irritation or rashes appear.

- Replace the cap after use.

- Keep out of reach of children

KEEP OUT OF REACH OF CHILDREN

Uses

Helps improve anti-wrinkle problem

Directions

After washing or shaving, apply 2-3 pumps of the lotion on your face and gently wipe your skin with it.

For extra moisture, pour some onto your palms and gently press onto your face